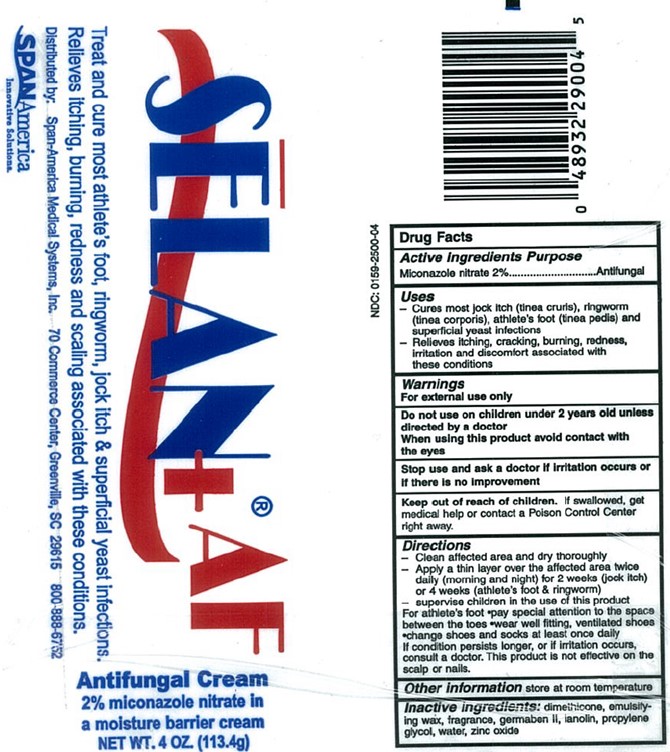 DRUG LABEL: Selan Antifungal
NDC: 0159-2500 | Form: CREAM
Manufacturer: Trividia Manufacturing Solutions, Inc
Category: otc | Type: HUMAN OTC DRUG LABEL
Date: 20251107

ACTIVE INGREDIENTS: MICONAZOLE NITRATE 2 g/100 g
INACTIVE INGREDIENTS: PROPYLENE GLYCOL; WATER; METHYLPARABEN; PROPYLPARABEN; DIAZOLIDINYL UREA; LANOLIN; DIMETHICONE 1000; ZINC OXIDE; POLAWAX POLYSORBATE

Selan AntiFungal

Active Ingredients

Miconazole nitrate 2%

Purpose

Antifungal

Uses

- Cures most jock itch (tinea cruris), ringworm (tinea corporis), athlete's foot (tinea pedis) and superficial yeast infections

- Relieves itching, cracking, burning, redness, irritation and discomfort associated with these conditions

Warnings

For external use only

Do not use on children under 2 years old unless directed by a doctor

When using this product avoid contact with the eyes

Stop use and ask a doctor if irritation occurs or if there is no improvement

Keep out of reach of children. If swallowed, get medical help or contact a Poison Control Center right away.

Directions

- Clean affected area and dry thoroughly

- Apply a thin layer over the affected area twice daily (morning and night) for 2 weeks (jock itch) or 4 weeks (athlete's foot & ringworm)

- Supervise children in the use of this product

For athlete's foot *pay special attention to the space between the toes *wear well fitting, ventilated shoes *change shoes and socks at least once daily

If condition persists longer, or if irritiation occurs, consult a doctor. This product is not effective on the scalp or nails.

Other information

store at room temperature

Inactive ingredients:

Dimethicone, emulsifying wax, fragrance, germaben II, lanolin, propylene glycol, water, zinc oxide